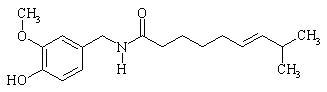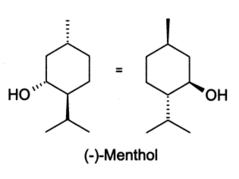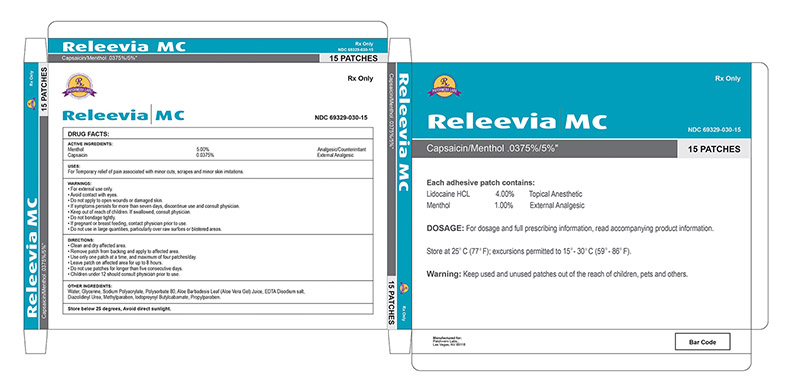 DRUG LABEL: Releevia MC
NDC: 69329-030 | Form: PATCH
Manufacturer: Patchwerx Labs, Inc
Category: prescription | Type: HUMAN PRESCRIPTION DRUG LABEL
Date: 20150308

ACTIVE INGREDIENTS: MENTHOL 5 g/100 g; CAPSAICIN .0375 g/100 g
INACTIVE INGREDIENTS: ALOE VERA LEAF; DIAZOLIDINYL UREA; EDETATE DISODIUM; GLYCERIN; IODOPROPYNYL BUTYLCARBAMATE; METHYLPARABEN; POLYSORBATE 80; PROPYLPARABEN; SODIUM POLYACRYLATE (2500000 MW); WATER

Releevia MC Patch

DESCRIPTION

Releevia MC Patch contains capsaicin and menthol in a localized dermal delivery system. The capsaicin in Releevia MC is a synthetic equivalent of the naturally occurring compound found in chili peppers. Capsaicin is soluble in alcohol, acetone, and ethyl acetate and very slightly soluble in water. The menthol is slightly soluble in water.

Releevia MC is a single-use patch stored in a foil pouch. Each Releevia MC patch is 8.3 cm x 12.5 cm (104 cm^2) and consists of a polyester backing film coated with a drug-containing silicone adhesive mixture, and covered with a removable polyester release liner.

The empirical formula for capsaicin is C18H27NO3, with a molecular weight of 305.42. The chemical compound capsaicin [(E)-8-methyl-N-vanillyl-6-nonenamide] is an activating ligand for transient receptor potential vanilloid 1 receptor (TRPV1) and it has the following structure:

The empirical formula for menthol is C10H20O, with a molecular weight of 156.27. The chemical compound menthol [(1 R,2 S,5 R)-2-isopropyl-5-methylcyclohexanol ] is an activating ligand for transient receptor potential cation channel subfamily M member 8 (TRPM8). It has the following structure:

Each Releevia MC Patch contains 0.0375% capsaicin (0.0375 grams of capsaicin per patch) and 5.00% menthol (5 grams of menthol per patch). The Releevia MC patch contains the following inactive ingredients: Aloe Barbadensis Leaf (Aloe Vera Gel) Juice, Diazolidinyl Urea, EDTA Disodiumm Salt, Glycerin, Iodoproynyl Butylcabamate, Methylparaben, Polysorbate 80, Propylparaben, Sodium Polyacrylate, and Water.

INDICATIONS AND USAGE

Releevia MC Patch is indicated for the temporary relief of minor aches and muscle pains associated with arthritis, simple backache, strains, muscle soreness and stiffness.

Releevia MC Patch is an external analgesic/counterirritant.

CONTRAINDICATIONS

Releevia MC Patch is contraindicated for those patients with a history of hypersensitivity to any of the components of the preparation.

WARNINGS

- For external use only.
- Use only as directed.
- Avoid contact with eyes and mucous membranes.
- Do not cover with bandage.
- Do not use on wounds or damaged skin.
- Consult physician for children under 12.
- Do not use if you are allergic to Menthol.
- Stop use and ask a doctor if conditions worsen, symptoms persist for more than 7 days or clear up and occur again within a few days or rash, itching or excessive skin irritation occurs.
- KEEP OUT OF REACH OF CHILDREN.

DOSAGE AND ADMINISTRATION

Releevia MC patch contains 0.0375% capsaicin and 5.00% menthol.

Instructions for Use

- Clean and dry affected area
- Cut open pouch and remove patch
- Remove protective film and apply directly to area of pain
- Apply to affected area not more than 3 times daily
- Wash hands with soap after applying patch
- Reseal pouch containing unused patches

Directions

Adults and children 12 years and over | - apply to affected area - change patch 1 to 2 times daily
Children under 12 years | - consult physician before use

HOW SUPPLIED

Releevia MC Patch is supplied in cartons with either 1 re-sealable pouch containing 5 patches or 3 re-sealable pouches each containing 5 patches each.

NDC 69329-030-05 5 Patches per carton

NDC 69329-030-15 15 Patches per carton

Storage: Store below 25°C. Avoid direct sunlight.

Manufactured for
Patchwerx Labs, Inc.
Las Vegas, NV 89118
800-590-8070